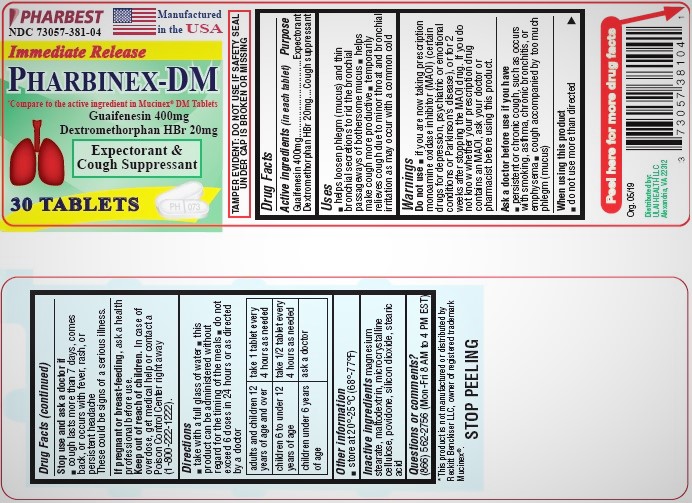 DRUG LABEL: Pharbinex-DM
NDC: 73057-381 | Form: TABLET
Manufacturer: Ulai Health LLC
Category: otc | Type: HUMAN OTC DRUG LABEL
Date: 20250120

ACTIVE INGREDIENTS: GUAIFENESIN 400 mg/1 1; DEXTROMETHORPHAN HYDROBROMIDE 20 mg/1 1
INACTIVE INGREDIENTS: MAGNESIUM STEARATE; MALTODEXTRIN; CELLULOSE, MICROCRYSTALLINE; POVIDONE K30; POVIDONE K90; SILICON DIOXIDE; STEARIC ACID

Drug Facts

Active ingredients (in each tablet)

Guaifenesin 400mg

Dextromethorphan HBr 20mg

Purpose

Expectorant

Cough suppressant

Uses

- helps loosen phlegm (mucus) and thin bronchial secretions to rid the bronchial passageways of bothersome mucus
- helps make cough more productive
- temporarily relieves cough due to minor throat and bronchial irritation as may occur with a common cold

Do not use

- if you are now taking a prescription monoamine oxidase inhibitor (MAOI) (certain drugs for depression, psychiatric or emotional conditions, or Parkinson’s disease), or for 2 weeks after stopping the MAOI drug. If you do not know whether your prescription drug contains an MAOI, ask your doctor or pharmacist before using this product.

Ask a doctor before use if you have

- persistent or chronic cough, such as occurs with smoking, asthma, chronic bronchitis, or emphysema
- cough accompanied by too much phlegm (mucus)

When using this product

- do not use more than directed

Stop use and ask a doctor if

- cough lasts more than 7 days, comes back, or occurs with fever, rash or persistent headache

These could be signs of a serious illness.

If pregnant or breast-feeding,

ask a health professional before use.

Keep out of reach of children.

In case of overdose, get medical help or contact a Poison Control Center right away (1-800-222-1222).

Directions

- take with a full glass of water
- this product can be administered without regard for the timing of the meals
- do not exceed 6 doses in 24 hours or as directed by a doctor

adults and children 12 years of age and over | take 1 tablet every 4 hours as needed
children 6 to under 12 years of age | take ½ tablet every 4 hours as needed
children under 6 years of age | ask a doctor

Other information

store at 20^0- 25^0C (68^0-77^0F)

Inactive ingredients

magnesium stearate, maltodextrin, microcrystalline celluclose, povidone, silicon dioxide, stearic acid

Questions or comments?

(866) 562-2756 (Mon-Fri 8 AM to 4 PM EST)

TAMPER EVIDENT: DO NOT USE IF SAFETY SEAL UNDER CAP IS BROKEN OR MISSING

*This product is not manufactured or distributed by Reckitt Benckiser LLC, owner of registered trademark Mucinex®

Distributed by:

ULAI HEALTH LLC.

Alexandria, VA 22312

PACKAGE LABEL

PHARBEST

NDC 73057-381-04

Manufactured in the USA

Immediate Release

PHARBINEX-DM

*Compare to the active ingredient in MUCINEX® DM Tablets

Guaifenesin 400mg

Dextromethorphan HBr 20mg

Expectorant &

Cough Suppressant

30 TABLETS